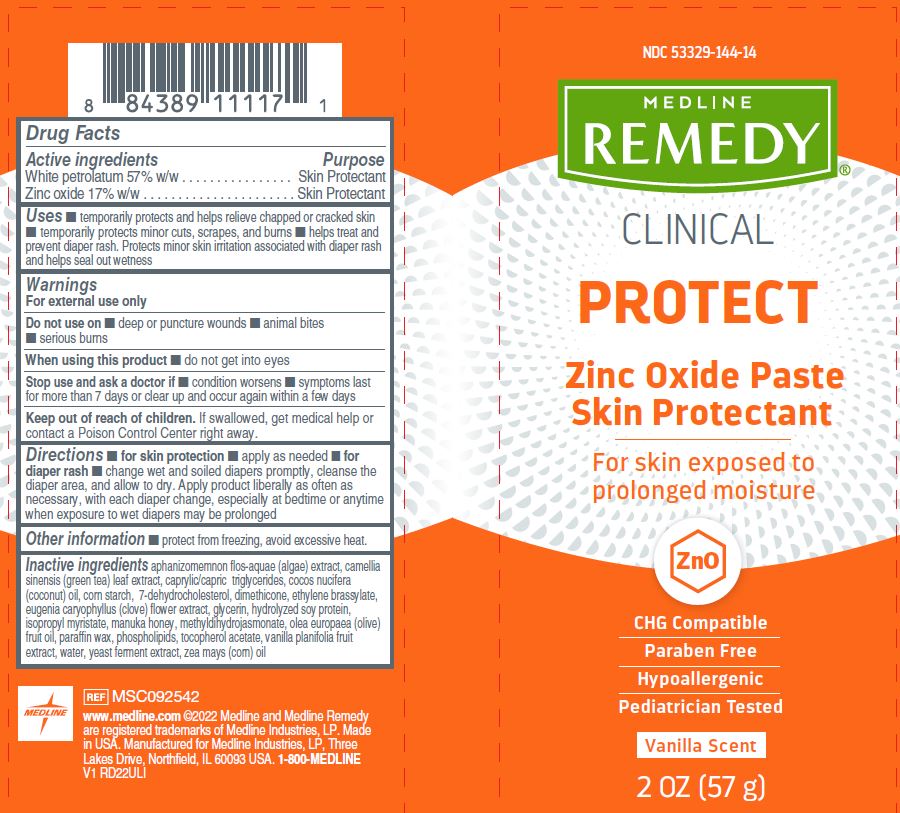 DRUG LABEL: Medline
NDC: 53329-144 | Form: PASTE
Manufacturer: Medline Industries, LP
Category: otc | Type: HUMAN OTC DRUG LABEL
Date: 20250821

ACTIVE INGREDIENTS: WHITE PETROLATUM 57 g/100 g; ZINC OXIDE 17 g/100 g
INACTIVE INGREDIENTS: VANILLA; OLIVE OIL; COCONUT OIL; APHANIZOMENON FLOSAQUAE; MEDIUM-CHAIN TRIGLYCERIDES; STARCH, CORN; ETHYLENE BRASSYLATE; CLOVE; GREEN TEA LEAF; DIMETHICONE; GLYCERIN; HYDROLYZED SOY PROTEIN (ENZYMATIC; 2000 MW); ISOPROPYL MYRISTATE; WATER; CORN OIL; HONEY; PARAFFIN; METHYL DIHYDROJASMONATE (SYNTHETIC); YEAST, UNSPECIFIED; LECITHIN, SOYBEAN; ALPHA-TOCOPHEROL ACETATE; 7-DEHYDROCHOLESTEROL

144 Remedy Clinical Zinc Oxide Paste

Active ingredients

White petrolatum 57% w/w

Zinc oxide 17% w/w

Purpose

Skin protectant

Uses

- temporarily protects and helps relieve chapped or cracked skin
- temporarily protects minor cuts, scrapes, and burns
- helps treat and prevent diaper rash. Protects minor skin irritation associated with diaper rash and helps seal out wetness

Warnings

For external use only.

Do not use on

- deep or puncture wounds
- animal bites
- serious burns

When using this product

- do not get into eyes

Stop use and ask a doctor if

- condition worsens
- symptoms last for more than 7 days or clear up and occur again within a few days

Keep out of reach of children.

If swallowed, get medical help or contact a Poison Control Center right away.

Directions

- for skin protection: apply as needed
- for diaper rash: change wet and soiled diapers promptly, cleanse the diaper area, and allow to dry. Apply product liberally as often as necessary, with each diaper change, especially at bedtime or anytime when exposure to wet diapers may be prolonged

Other information

- protect from freezing, avoid excessive heat

Inactive ingredients

aphanizomemnon flos-aquae (algae) extract, camellia sinensis (green tea) leaf extract, caprylic/capric triglycerides, cocos nucifera (coconut) oil, corn starch, 7-dehydrocholesterol, dimethicone, ethylene brassylate, eugenia caryophyllus (clove) flower extract, glycerin, hydrolyzed soy protein, isopropyl myristate, manuka honey, methyldihydrojasmonate, olea europaea (olive) fruit oil, paraffin wax, phospholipids, tocopherol acetate, vanilla planifolia fruit extract, water, yeast ferment extract, zea mays (corn) oil

Manufacturing Information

Manufactured for:

Medline Industries, LP

Three Lakes Drive, Northfield, IL 60093 USA

Made in USA.

www.medline.com

1-800-MEDLINE (633-5463)

REF: MSC092542

V1 RD22ULI